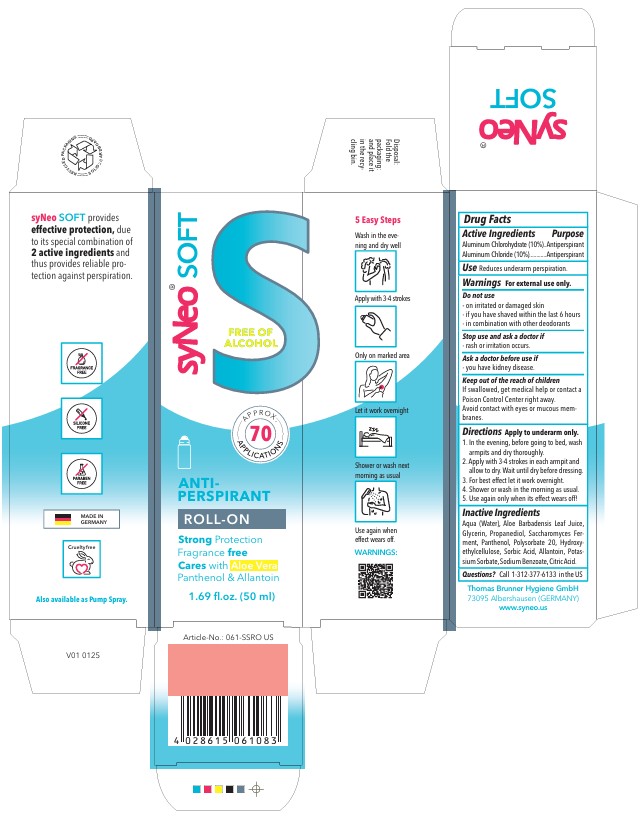 DRUG LABEL: SyNeo SOFT ANTI-PERSPIRANT
NDC: 85118-006 | Form: STICK
Manufacturer: Thomas Brunner Hygiene GmbH
Category: otc | Type: HUMAN OTC DRUG LABEL
Date: 20250227

ACTIVE INGREDIENTS: ALUMINUM CHLOROHYDRATE 10 g/100 mL; ALUMINUM CHLORIDE 10 g/100 mL
INACTIVE INGREDIENTS: ALOE BARBADENSIS LEAF JUICE; PANTHENOL; SODIUM BENZOATE; WATER; POLYSORBATE 20; SORBIC ACID; GLYCERIN; PROPANEDIOL; SACCHAROMYCES LYSATE; CITRIC ACID; HYDROXYETHYLCELLULOSE; POTASSIUM SORBATE; ALLANTOIN

SyNeo SOFT ANTI-PERSPIRANT ROLL-ON

Drug Facts

ACTIVE INGREDIENT

Active Ingredients | Purpose
Aluminum Chlorohydrate (10%) | Antiperspirant
Aluminum Chloride (10%) | Antiperspirant

Use

Reduces underarm perspiration.

WARNINGS

For external use only.

Do not use

- on irritated or damaged skin
- if you have shaved within the last 6 hours
- in combination with other deodorants

Stop use and ask a doctor if

- rash or irritation occurs.

Ask a doctor before use if

- you have kidney disease.

Keep out of the reach of children

If swallowed, get medical help or contact a Poison Control Center right away.

Avoid contact with eyes or mucous membranes.

Directions

Apply to underarm only.

1. In the evening, before going to bed, wash armpits and dry thoroughly.
2. Apply with 3-4 strokes in each armpit and allow to dry. Wait until dry before dressing.
3. For best effect let it work overnight.
4. Shower or wash in the morning as usual.
5. Use again only when its effect wears off!

INACTIVE INGREDIENT

Aqua (Water), Aloe Barbadensis Leaf Juice, Glycerin, Propanediol, Saccharomyces Ferment, Panthenol, Polysorbate 20, Hydroxyethylcellulose, Sorbic Acid, Allantoin, Potassium Sorbate, Sodium Benzoate, Citric Acid.

Questions?

Questions? Call 1-312-377-6133 in the US

SyNeo SOFT ANTI-PERSPIRANT ROLL-ON

SyNeo SOFT

FREE OF ALCOHOL

APPROX. 70 APPLICATIONS

ANTI-

PERSPIRANT

ROLL-ON

Strong Protection

Fragrance free

Cares with Aloe Vera

Panthenol & Allantoin

1.69 fl.oz. (50 ml)